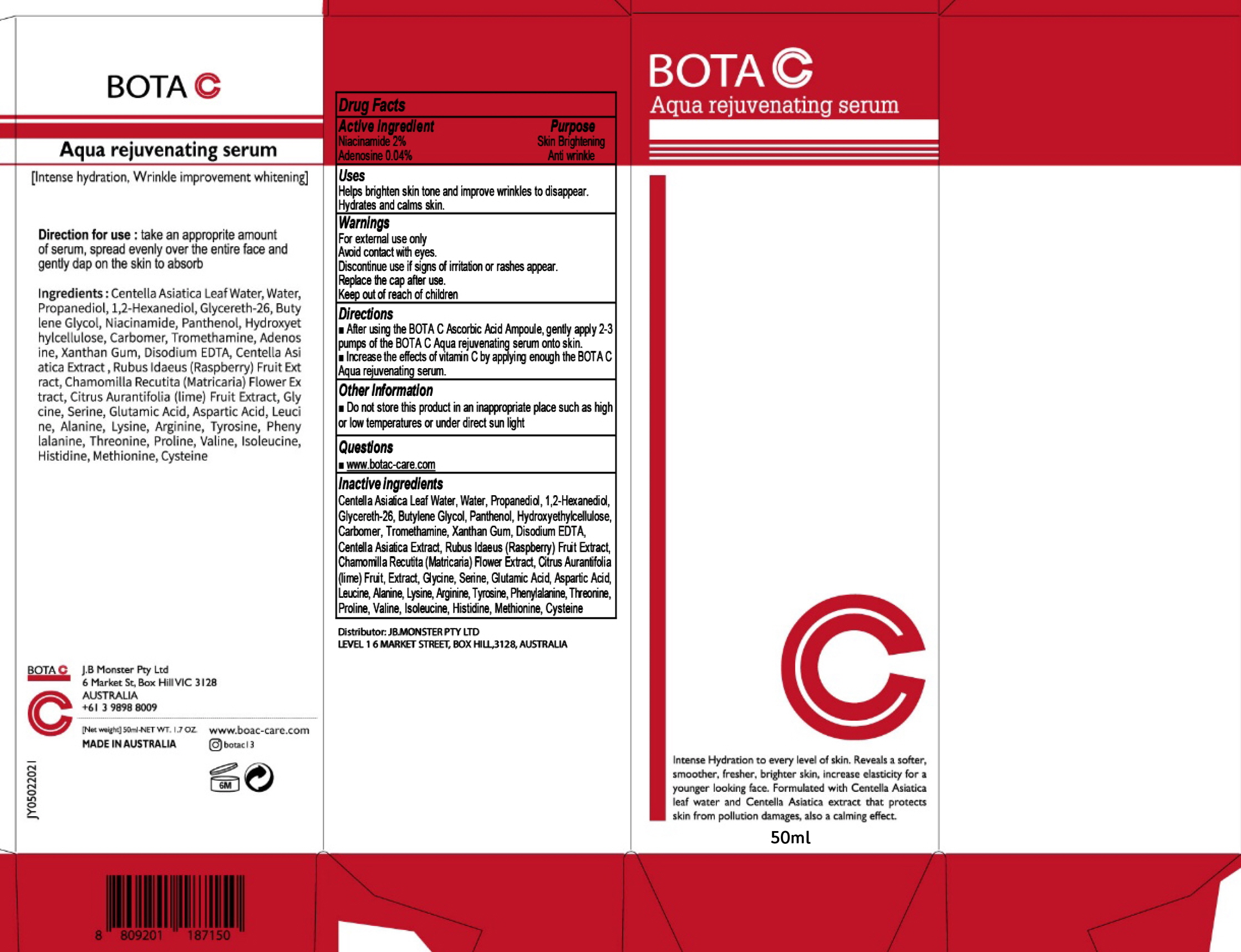 DRUG LABEL: BOTA C Aqua rejuvenating serum
NDC: 82399-020 | Form: LIQUID
Manufacturer: JB.MONSTER PTY LTD
Category: otc | Type: HUMAN OTC DRUG LABEL
Date: 20211231

ACTIVE INGREDIENTS: Niacinamide 1.0 g/50 mL; Adenosine 0.02 g/50 mL
INACTIVE INGREDIENTS: CENTELLA ASIATICA LEAF; Water; Propanediol

ACTIVE INGREDIENTS

Niacinamide 2%
Adenosine 0.04%

INACTIVE INGREDIENTS

Centella Asiatica Leaf Water, Water, Propanediol, 1,2-Hexanediol, Glycereth-26, Butylene Glycol, Panthenol, Hydroxyethylcellulose, Carbomer, Tromethamine, Xanthan Gum, Disodium EDTA, Centella Asiatica Extract, Rubus Idaeus (Raspberry) Fruit Extract, Chamomilla Recutita (Matricaria) Flower Extract, Citrus Aurantifolia (lime) Fruit, Extract, Glycine, Serine, Glutamic Acid, Aspartic Acid, Leucine, Alanine, Lysine, Arginine, Tyrosine, Phenylalanine, Threonine, Proline, Valine, Isoleucine, Histidine, Methionine, Cysteine

PURPOSE

Skin Brightening
Anti wrinkle

Uses

■ Helps brighten skin tone and improve wrinkles to disappear.
■ Hydrates and calms skin.

WARNINGS

For external use only
Avoid contact with eyes.
Discontinue use if signs of irritation or rashes appear.
Replace the cap after use.
Keep out of reach of children

KEEP OUT OF REACH OF CHILDREN

Directions

■ After using the BOTA C Ascorbic Acid Ampoule, gently apply 2-3 pumps of the BOTA C Aqua rejuvenating serum onto skin.
■ Increase the effects of vitamin C by applying enough the BOTA C Aqua rejuvenating serum.

Other Information

■ Do not store this product in an inappropriate place such as high or low temperatures or under direct sun light

Questions

■ www.botac-care.com